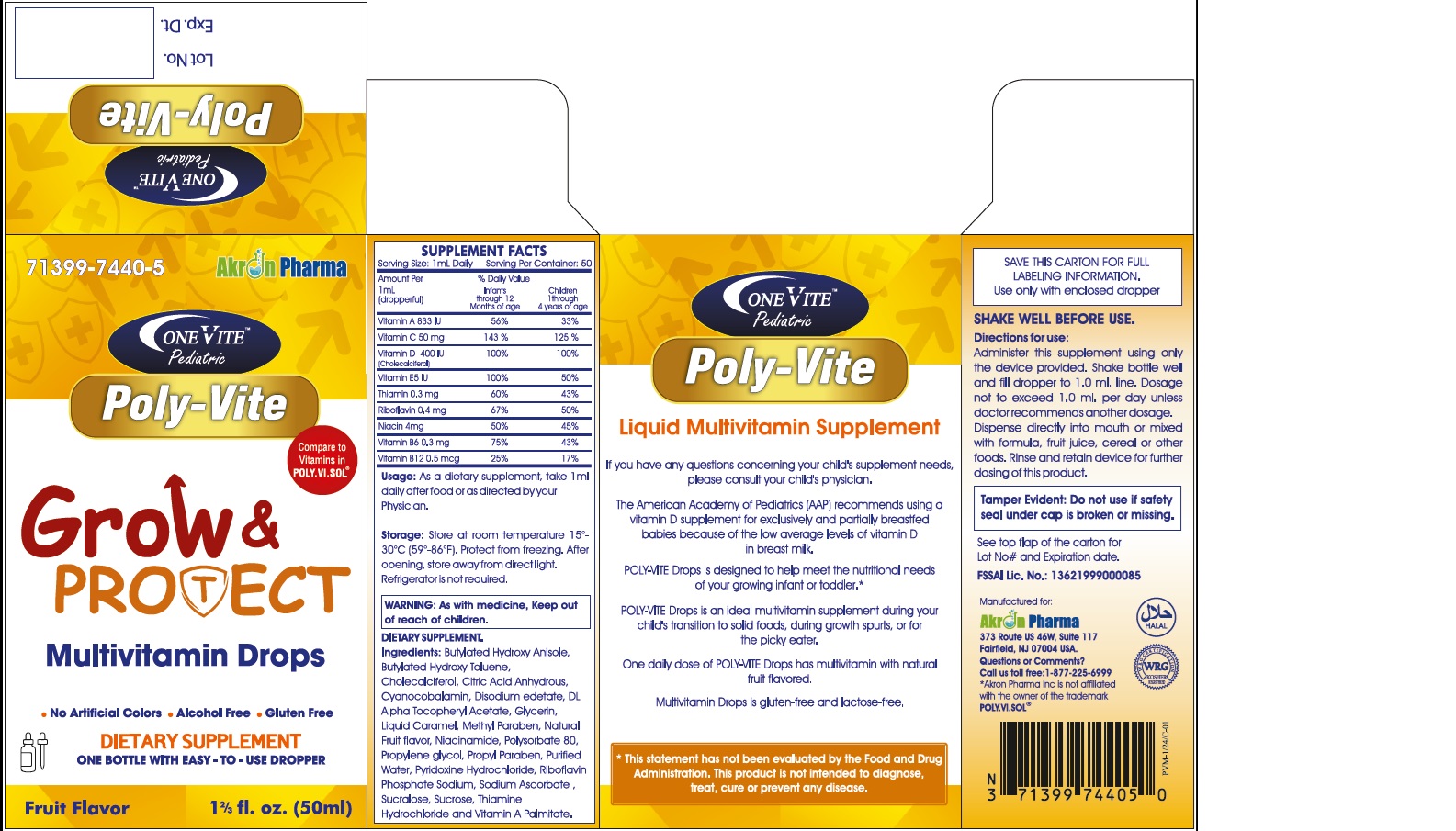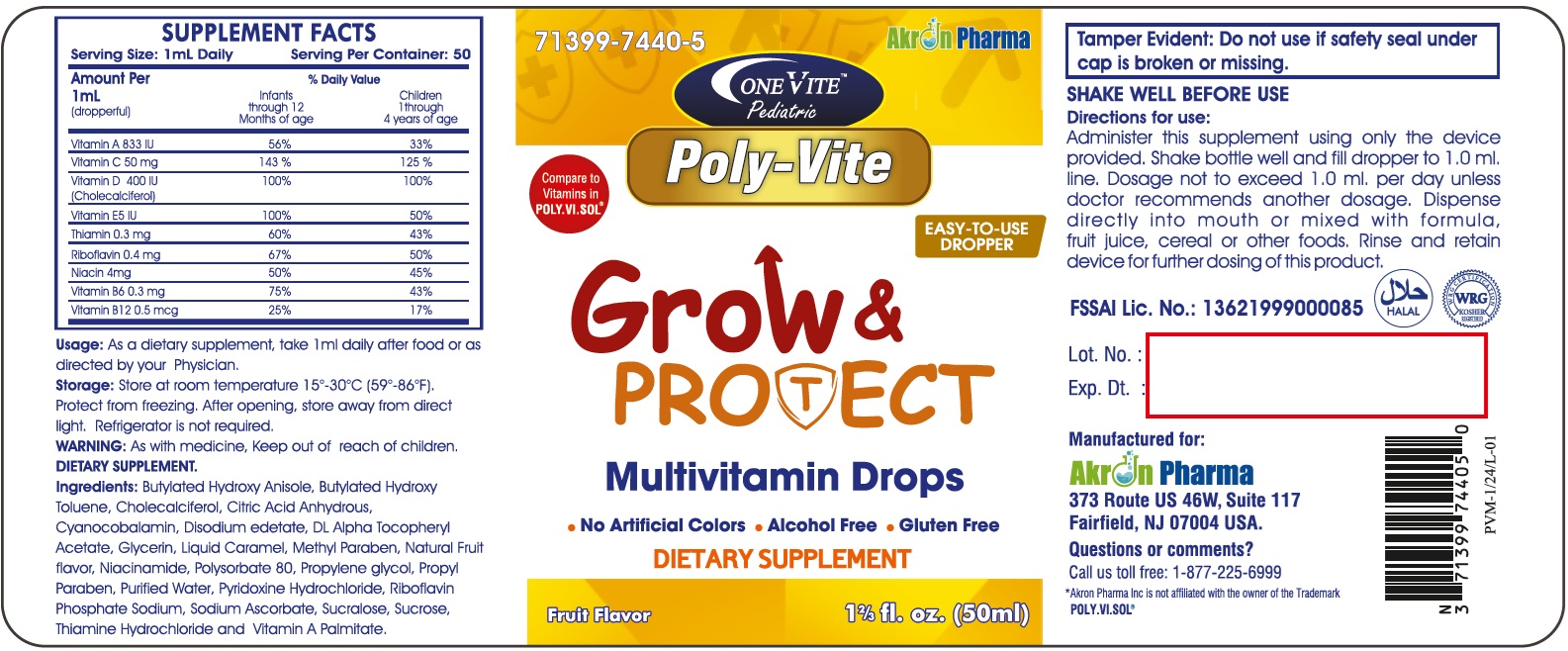 DRUG LABEL: Poly-Vite Pediatric Oral Solution
NDC: 71399-7440 | Form: SOLUTION
Manufacturer: Akron Pharma
Category: other | Type: DIETARY SUPPLEMENT
Date: 20250224

ACTIVE INGREDIENTS: VITAMIN A PALMITATE .25 mg/1 mL; SODIUM ASCORBATE 50 mg/1 mL; CHOLECALCIFEROL .01 mg/1 mL; ALPHA-TOCOPHEROL ACETATE 5 mg/1 mL; THIAMINE HYDROCHLORIDE .3 mg/1 mL; RIBOFLAVIN 5'-PHOSPHATE SODIUM .4 mg/1 mL; NIACINAMIDE 4 mg/1 mL; PYRIDOXINE HYDROCHLORIDE .3 mg/1 mL; CYANOCOBALAMIN .5 ug/1 mL
INACTIVE INGREDIENTS: SUCROSE; GLYCERIN; PROPYLENE GLYCOL; POLYSORBATE 80; METHYLPARABEN; ANHYDROUS CITRIC ACID; SACCHARIN SODIUM; EDETATE DISODIUM; PROPYLPARABEN; CARAMEL; BUTYLATED HYDROXYANISOLE; BUTYLATED HYDROXYTOLUENE; WATER

OneVITE Pediatric
POLY-VITE Drops
Grow and Protect

STATEMENT OF IDENTITY

Supplement Facts

Serving size: 1 mL Daily

Serving per container: 50

Amount per 1 mL (dropperful) % Daily Value

Infants through 12 Months of age Children 1 through 4 Years of age

Vitamin A 250 mcg 56% 33%

Vitamin C 50 mg 143% 125%

Vitamin D3 10 mcg 100% 100%

Vitamin E 5 mg 100% 50%

Thiamin 0.3 mg 60% 43%

Riboflavin 0.4 mg 67% 50%

Niacin 4 mg 50% 45%

Vitamin B6 0.3 mg 75% 43%

Vitamin B12 0.5 mcg 25% 17%

HEALTH CLAIM

POLY-VITE Drops is designed to help meet the nutritional needs of your growing infant or toddler.*

POLY-VITE Drops is an ideal multivitamin supplement during your child's transition to solid foods, during growth spurts, or for the picky eater.

* This statement has not been evaluated by the Food and Drug Administration. This product is not intended to diagnose, treat, cure, or prevent any disease.

SAFE HANDLING WARNING

Storage: Store at room temperature 15º -30ºC(59º -86ºF). Protect from freezing. After opening, store away from direct light. Refrigerator is not required.

WARNINGS

WARNING: As with medicine, Keep out of reach of children.

PRECAUTIONS

SHAKE WELL BEFORE USE.

DOSAGE AND ADMINISTRATION

Directions for use:

Administer this supplement using only the device provided. Shake bottle well and fill dropper to 1.0 ml. line. Dosage not to exceed 1.0 ml. per day unless doctor recommends another dosage. Dispense directly into mouth or mixed with formula, fruit juice, cereal, or other foods. Rinse and retain device for further dosing of this product.